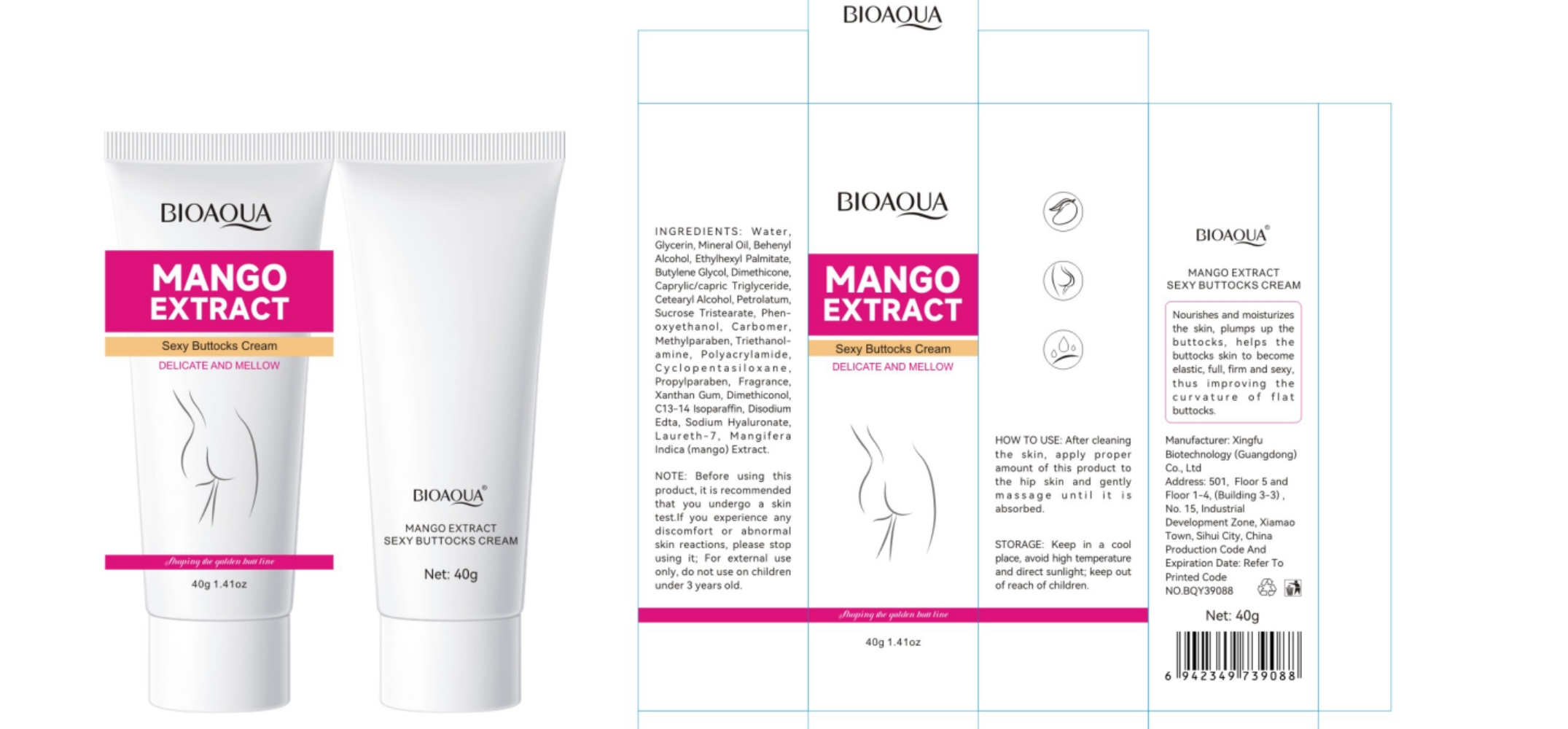 DRUG LABEL: bioaouamangoextractsexybuttockscream
NDC: 84372-045 | Form: LOTION
Manufacturer: Shenzhen Zhumeng Times Technology Co., Ltd.
Category: otc | Type: HUMAN OTC DRUG LABEL
Date: 20240904

ACTIVE INGREDIENTS: MEDIUM-CHAIN TRIGLYCERIDES 3 g/40 g
INACTIVE INGREDIENTS: HYALURONATE SODIUM; METHYLPARABEN; ETHYLHEXYL PALMITATE; PETROLATUM; EDETATE DISODIUM; MANGIFERA INDICA BARK; MINERAL OIL; BUTYLENE GLYCOL; DIMETHICONE; LAURETH-7; PROPYLPARABEN; WATER; FRAGRANCE 13576; DOCOSANOL; SUCROSE TRISTEARATE; IVERMECTIN; CETOSTEARYL ALCOHOL; C13-14 ISOPARAFFIN; CYCLOMETHICONE 5; TROLAMINE; POLYACRYLAMIDE (1500 MW); GLYCERIN; DIMETHICONE 6; PHENOXYETHANOL; XANTHAN GUM

Active ingredients

Caprylic/Capric Triglyceride 3%

Purpose

Nourishes and moisturizes
the skin,plumps up the
buttocks,helps the
buttocks skin to become
elastic,full,firm and sexy,
thus improving the
curvature of flat
buttocks.

Uses

After cleaning
the skin,apply proper
amount of this product to
the hip skin and gently
massage until it is
absorbed.

Warnings

Before using this
product, it is recommended
that you undergo a skin
test.If you experience any
discomfort or abnormal
skin reactions, please stop
using it;For external use
only,do not use on children
under3 years old.

Dosage and administration

For external use only.

Do not use

Stop use and ask a doctor if

chest pain, rapid heartbeat, faintness, or dizziness occurs

sudden, unexplained weight gain occurs

your hands or feet swell

scalp irritation or redness occurs

unwanted facial hair growth occurs

you do not see hair regrowth in 4 months

May be harmful if used when pregnant or breast-feeding.

Keep out of reach of children, lf swallowed, get medical help or contact a Poison Control Center right away.

When using section

After cleaning
the skin,apply proper
amount of this product to
the hip skin and gently
massage until it is
absorbed.

stop use

on broken or irritated scalp

If sxralowed, get medical help or contact a Poison Conirol Cenler ngiht away.

Inactive ingredients

Water,

Glycerin,Mineral Oil,BehenylAlcohol,EthyIhexyl Palmitate,Butylene Glycol,Dimethicone,

Cetearyl Alcohol,Petrolatum,Sucrose Tristearate,

Phen-oxyethanol,Carbomer,Methylparaben,Triethanol-amine, Polyacrylamide,

Cyclopentasiloxane,Propylparaben,Fragrance,Xanthan Gum,Dimethiconol,

C13-14 Isoparaffin,DisodiumEdta,Laureth-7,

MangiferaIndica(mango)Extract.